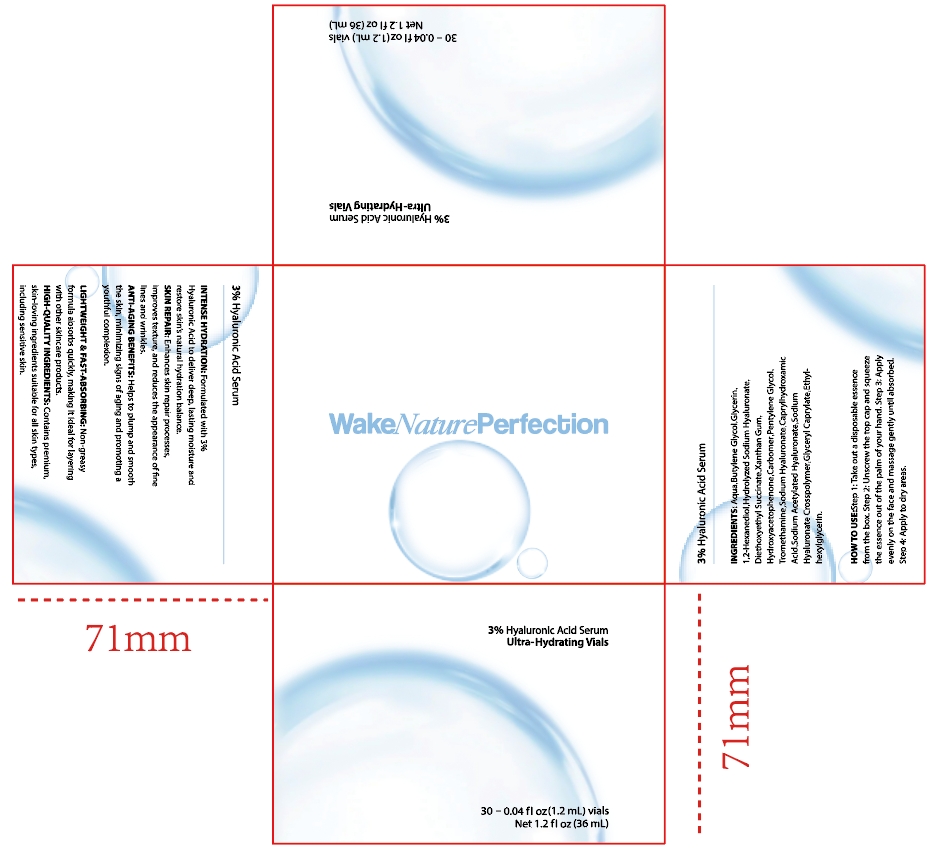 DRUG LABEL: 3% Hyaluronic Acid Serum
NDC: 84732-096 | Form: LIQUID
Manufacturer: Dongguan Haiyi Technology Co.,Ltd.
Category: otc | Type: HUMAN OTC DRUG LABEL
Date: 20241205

ACTIVE INGREDIENTS: HYALURONIC ACID 3 dL/100 mL
INACTIVE INGREDIENTS: BUTYLENE GLYCOL; 1,2-HEXANEDIOL; PENTYLENE GLYCOL; HYDROXYACETOPHENONE; CARBOMER; XANTHAN GUM; WATER; DIETHOXYETHYL SUCCINATE; GLYCERIN

Active ingredient

3% Hyaluronic Acid

Inactive ingredient

Aqua
Butylene Glycol
Glycerin
1,2-Hexanediol
Hydrolyzed Sodium Hyaluronate
Diethoxyethyl Succinate
Xanthan Gum
Hydroxyacetophenone
Carbomer
Pentylene Glycol
Tromethamine
Sodium Hyaluronate
Caprylhydroxamic Acid
Sodium Acetylated Hyaluronate
Glyceryl Caprylate

Purpose section

1. INTENSE HYDRATON: Formulated with 3%Hyaluronic Acid to deliver deep, lasting moisture andrestore skin's natral hydration balance

2. SKIN REPAIR: Enhances skin repair processes,improves texture, and reduces the appearance of fhelines and wrinkles.

3. AN'TI-AGING BENEFITS: Helps to plump and smooththe skin, minimizing signs ofaging and promoting ayouthful complexion.

4.LIGHTWEIGHT&FAST-ABSORBING: Non-greasyfomula absorbs quickly, making it ideal for ayeringwith other skincare prodc.

5.HIGH-QUALITYINGREDIENTSContains premium,skin-loving ingredients suitable for all skin types,including sensitive skin.

Warning

1).For external use only, avoid directcontact with eyes, lf you feel anydiscomfort, stop using itand wash it with plenty of water, In severe cases,pleaseseek medical attention in time.

2). Not allowed to be used ondamaged skin,

stop use

This product may cause allergic reactions in asmall number of people.
lf youexperience any discomfort,please stop using it immediately.

not use

Not suitable for use by children, pregnantor breast feeding people.

OUT OF CHILDREN

KEEP THE PRODUCT OUT OF REACH OF CHILDREN to

HOW TO USE

Step 1:Take out a disposable essencefrom the box,

Step 2: Unscrew the top cap and squeezethe essence out of the palm ofyour hand.

Step 3: Applyevenly on the face and massage gently until absorbed.

Step 4: Apply to dry areas.

Dosage

take an appropriateamount,Use 2-3 times a week